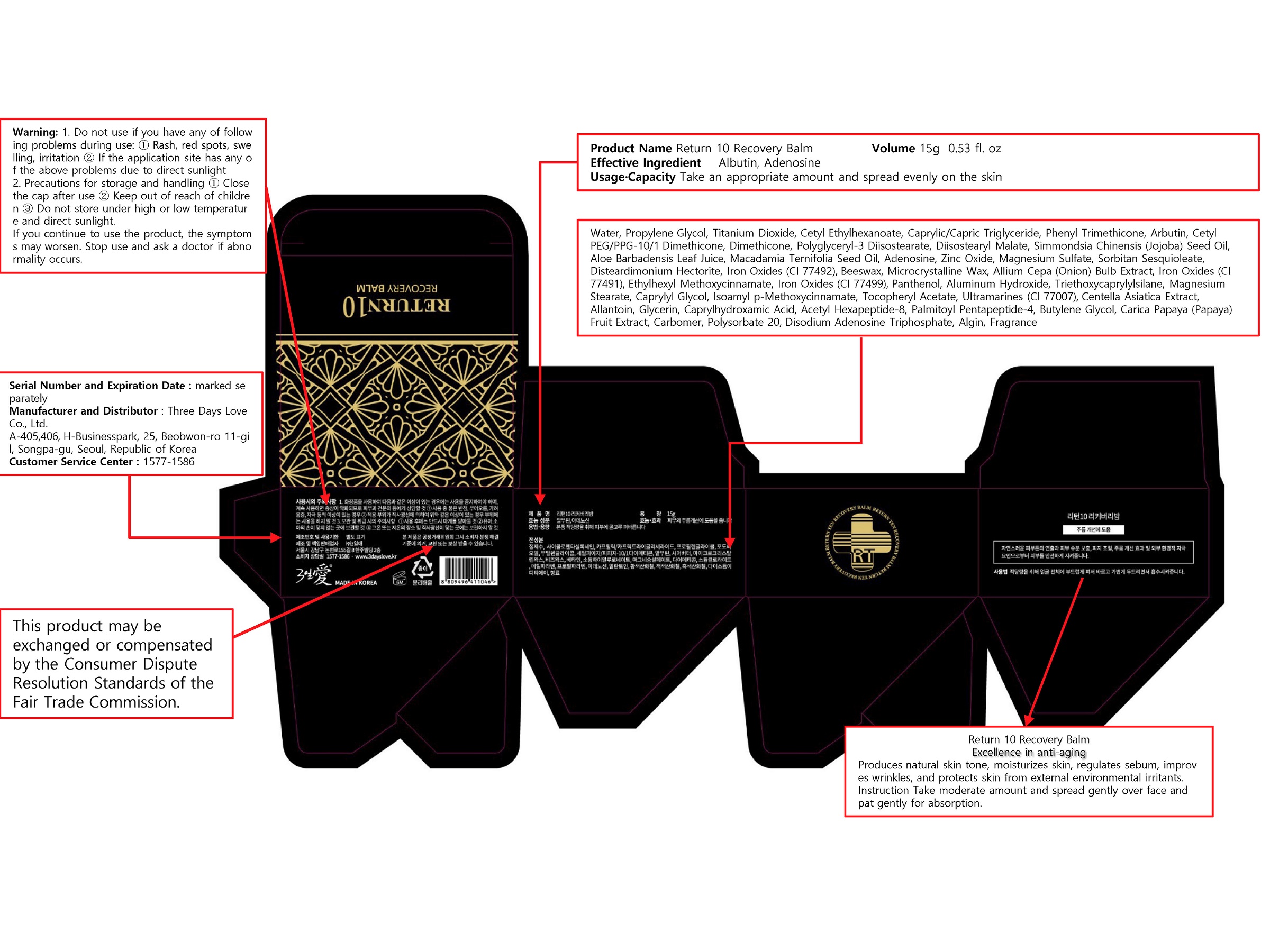 DRUG LABEL: Return 10 Recovery Balm
NDC: 72368-0005 | Form: CREAM
Manufacturer: Threedayslove Co., Ltd.
Category: otc | Type: HUMAN OTC DRUG LABEL
Date: 20200121

ACTIVE INGREDIENTS: ADENOSINE 0.04 g/100 g; ARBUTIN 2 g/100 g
INACTIVE INGREDIENTS: DIMETHICONE; WATER; BUTYLENE GLYCOL

Drug Facts

ACTIVE INGREDIENT

Arbutin, Adenosine

INACTIVE INGREDIENT

Water
Propylene Glycol
Titanium Dioxide
Cetyl Ethylhexanoate
Ethylhexyl Methoxycinnamate
Caprylic/Capric Triglyceride
Phenyl Trimethicone
Isoamyl p-Methoxycinnamate
Cetyl PEG/PPG-10/1 Dimethicone
Dimethicone
Polyglyceryl-3 Diisostearate
Diisostearyl Malate
Simmondsia Chinensis (Jojoba) Seed Oil
Aloe Barbadensis Leaf Juice
Macadamia Ternifolia Seed Oil
Zinc Oxide
Magnesium Sulfate
Sorbitan Sesquioleate
Disteardimonium Hectorite
Iron Oxides (CI 77492)
Beeswax
Microcrystalline Wax
Allium Cepa (Onion) Bulb Extract
Snail Secretion Filtrate
Iron Oxides (CI 77491)
Iron Oxides (CI 77499)
Panthenol
Aluminum Hydroxide
Triethoxycaprylylsilane
Magnesium Stearate
Caprylyl Glycol
Tocopheryl Acetate
Ultramarines (CI 77007)
Centella Asiatica Extract
Allantoin
Glycerin
Caprylhydroxamic Acid
Acetyl Hexapeptide-8
Butylene Glycol
Carica Papaya (Papaya) Fruit Extract
Carbomer
Polysorbate 20
Disodium Adenosine Triphosphate
Algin
Palmitoyl Pentapeptide-4
Fragrance

PURPOSE

Excellence in anti-aging

keep out of reach of the children

INDICATIONS AND USAGE

Take an appropriate amount and spread evenly on the skin

WARNINGS

Warning: 1. Do not use if you have any of following problems during use: ① Rash, red spots, swelling, irritation ② If the application site has any of the above problems due to direct sunlight

2. Precautions for storage and handling ① Close the cap after use ② Keep out of reach of children ③ Do not store under high or low temperature and direct sunlight.

If you continue to use the product, the symptoms may worsen. Stop use and ask a doctor if abnormality occurs.

DOSAGE AND ADMINISTRATION

for external use only